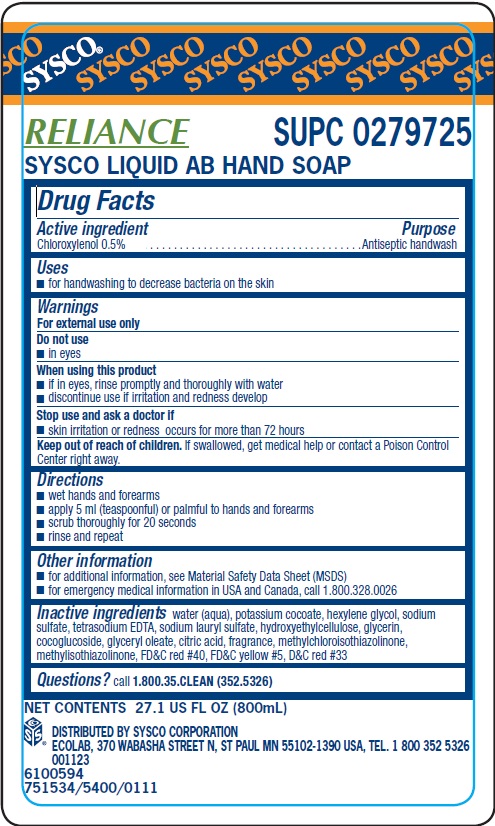 DRUG LABEL: Sysco
NDC: 47593-479 | Form: SOLUTION
Manufacturer: Ecolab Inc.
Category: otc | Type: HUMAN OTC DRUG LABEL
Date: 20240426

ACTIVE INGREDIENTS: CHLOROXYLENOL 0.5 mg/100 mL
INACTIVE INGREDIENTS: WATER ; POTASSIUM COCOATE; HEXYLENE GLYCOL; SODIUM SULFATE; EDETATE SODIUM; SODIUM LAURYL SULFATE; HYDROXYETHYL CELLULOSE (2000 CPS AT 1%); GLYCERIN; COCO GLUCOSIDE; GLYCERYL OLEATE; CITRIC ACID MONOHYDRATE; METHYLCHLOROISOTHIAZOLINONE; METHYLISOTHIAZOLINONE; FD&C RED NO. 40; FD&C YELLOW NO. 5; D&C RED NO. 33

Drug Facts

Active ingredient

Chloroxylenol 0.5%

Purpose

Antiseptic handwash

Uses

- for handwashing to decrease bacteria on the skin

Warnings

For external use only

Do not use

- in eyes

When using this product

- if in eyes, rinse promptly and thoroughly with water
- discontinue use if irritation and redness develop

Stop use and ask doctor if

- skin irritation or redness occurs for more than 72 hours

KEEP OUT OF REACH OF CHILDREN

Keep our of reach of children. If swallowed, get medical help or contact a Poison Control Center right away.

Directions

- wet hands and forearms
- apply 5 ml (teaspoonful) or palmful to hands and forearms
- scrub thoroughly for 20 seconds
- rinse and repeat

Other information

- for additional information, see Material Safety Data Sheet (MSDS)
- for emergency medical information in USA and Canada, call 1.800.328.0026

INACTIVE INGREDIENT

Inactive ingredients water (aqua), potassium cocoate, hexylene glycol, sodium sulfate, tetrasodium EDTA, sodium lauryl sulfate, hydroxyehtylcellulose, glycerin, cocoglucoside, glyceryl oleate, citric acid, fragrance, methylchloroisothiazolinone, methylisothiazolinone, FDC red 40, FDC yellow 5, DC red 33

Questions? call 1.800.35.CLEAN (352.5326)

Principal display panel and representative label

SYSCO

RELIANCE SUPC 0279725

SYSCO LIQUID AB HAND SOAP

NET CONTENTS 27.1 US FL OZ (800mL)

DISTRIBUTED BY SYSCO CORPORATION

ECOLAB, 370 WABASHA STREET N, ST PAUL MN 55102-1390 USA, TEL. 1800 352 5326

001123

65100594

751534/5400/0111